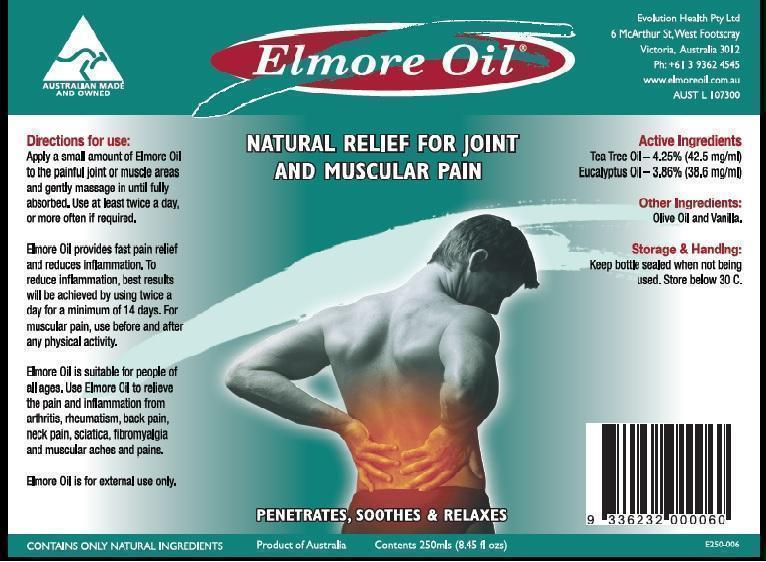 DRUG LABEL: Elmore Oil
NDC: 69594-002 | Form: OIL
Manufacturer: Ultra Mix (Aust) Pty Ltd 
Category: otc | Type: HUMAN OTC DRUG LABEL
Date: 20160405

ACTIVE INGREDIENTS: Eucalyptus Oil 38.6 mg/1 mL; Tea Tree Oil 42.5 mg/1 mL
INACTIVE INGREDIENTS: OLIVE OIL; VANILLIN

Elmore Oil

Actives

Tea Tree Oil (Melaleuca Alternifolia) - 4.25% (42.5 mg/ml)
Eucalyptus Oil (Eucalyptus radiata) - 3.86% (38.6 mg/ml)

Purpose

Massage Oil to assist with relief of joint and muscle pain

Indication and Usage

Temporary relief of joint and muscle pain, including lower back pain

Dosage and Administration

Apply a small amount of Elmore Oil to the pain affected area and gently massage in until fully absorbed. Use before and after activity for maximum relief.

Warnings

For external use only.
Keep out of reach of children